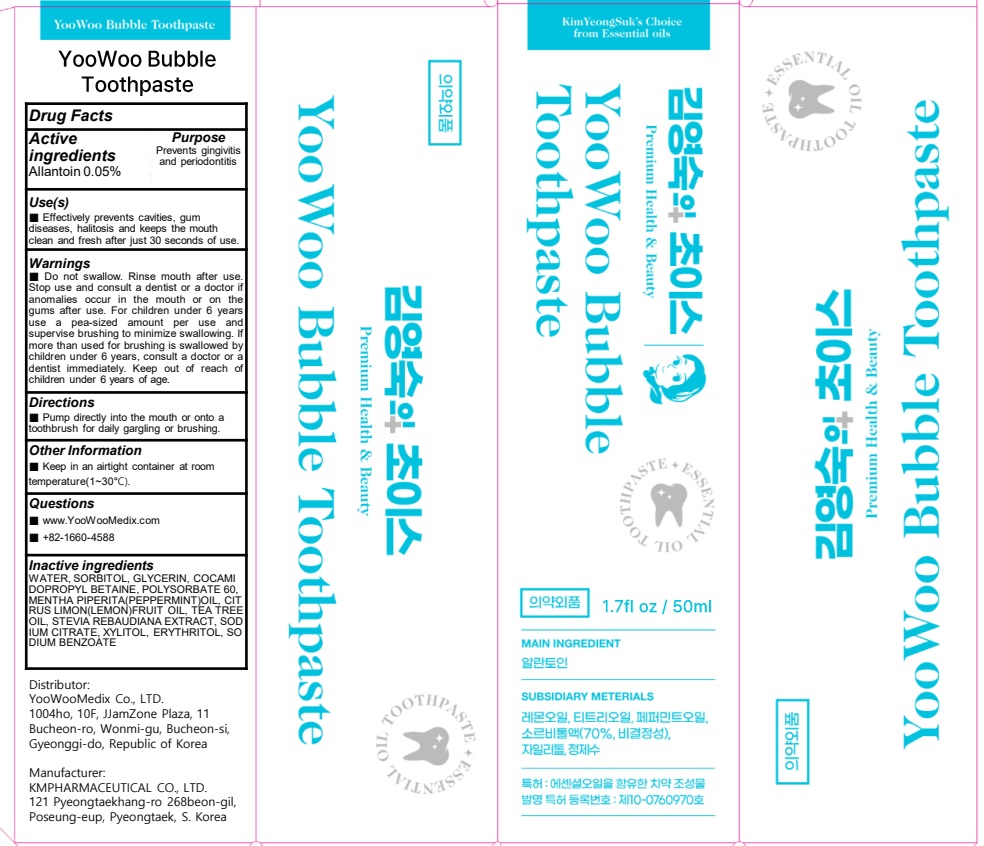 DRUG LABEL: YooWoo Bubble Tooth
NDC: 84875-020 | Form: PASTE, DENTIFRICE
Manufacturer: YOOWOOMEDIX
Category: otc | Type: HUMAN OTC DRUG LABEL
Date: 20241031

ACTIVE INGREDIENTS: ALLANTOIN 0.05 g/100 mL
INACTIVE INGREDIENTS: WATER; SORBITOL; COCAMIDOPROPYL BETAINE; GLYCERIN

ACTIVE INGREDIENT

Allantoin 0.05%

INACTIVE INGREDIENT

WATER, SORBITOL, GLYCERIN, COCAMIDOPROPYL BETAINE, POLYSORBATE 60, MENTHA PIPERITA(PEPPERMINT)OIL, CITRUS LIMON(LEMON)FRUIT OIL, TEA TREE OIL, STEVIA REBAUDIANA EXTRACT, SODIUM CITRATE, XYLITOL, ERYTHRITOL, SODIUM BENZOATE

PURPOSE

Prevents gingivitis and periodontitis

WARNINGS

■ Do not swallow. Rinse mouth after use. Stop use and consult a dentist or a doctor if anomalies occur in the mouth or on the gums after use. For children under 6 years use a pea-sized amount per use and supervise brushing to minimize swallowing. If more than used for brushing is swallowed by children under 6 years, consult a doctor or a dentist immediately. Keep out of reach of children under 6 years of age.

Keep out of reach of children under 6 years of age.

INDICATIONS AND USAGE

Use(s)

■ Effectively prevents cavities, gum diseases, halitosis and keeps the mouth clean and fresh after just 30 seconds of use.

Directions

■ Pump directly into the mouth or onto a toothbrush for daily gargling or brushing.

Other Information

■ Keep in an airtight container at room temperature(1~30°C).

QUESTIONS

■ www.YooWooMedix.com

■ 82-2-1660-4588